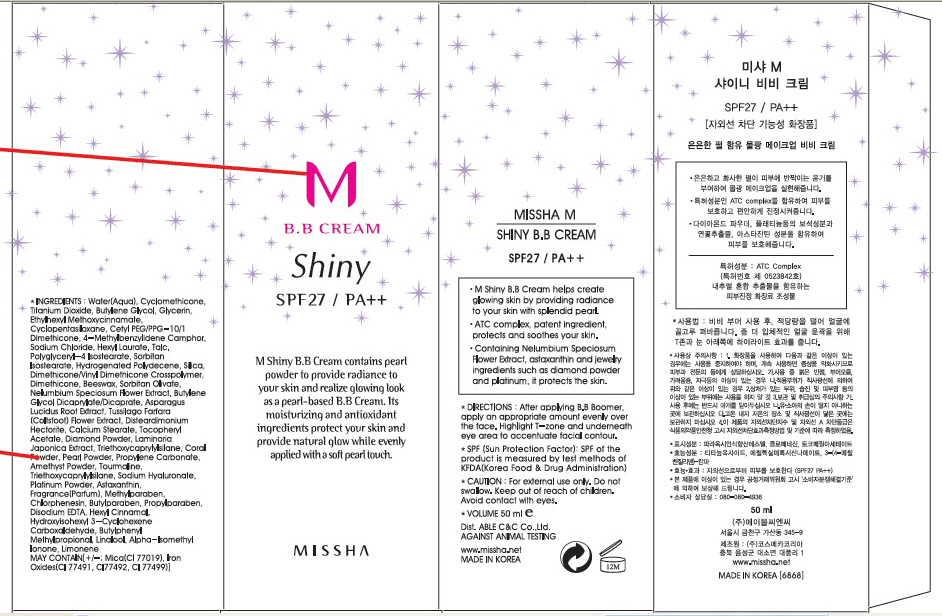 DRUG LABEL: MISSHA M SHINY BB
NDC: 13733-003 | Form: CREAM
Manufacturer: ABLE C&C CO., LTD.
Category: otc | Type: HUMAN OTC DRUG LABEL
Date: 20100520

ACTIVE INGREDIENTS: TITANIUM DIOXIDE 3.77 mL/50 mL

Drug Facts

Active Ingredient: TITANIUM DIOXIDE

Inactive Ingredients:
Water, Cyclomethicone, Butylene Glycol, Glycerin, Ethylhexyl Methoxycinnamate, Cyclopentasiloxane, Cetyl PEG/PPG-10/1 Dimethicone, 4-Methylbenzylidene Camphor,
Sodium Chloride, Mica, Hexyl Laurate, Talc, Polyglyceryl-4 Isostearate, Sorbitan Isostearate, Hydrogenated Polydecene, Silica, Dimethicone/Vinyl Dimethicone Crosspolymer,
Dimethicone, Iron Oxides, Beeswax, Sorbitan Olivate, Nelumbium Speciosum Flower Extract, Butylene Glycol Dicaprylate/Dicaprate, Asparagus Lucidus Root Extract,
Tussilago Farfara (Coltsfoot) Flower Extract, Disteardimonium Hectorite, Calcium Stearate, Methylparaben, Chlorphenesin, Tocopheryl Acetate, Butylparaben,
Propylparaben, Diamond Powder, Laminaria Japonica Extract, Fragrance, Triethoxycaprylylsilane, Coral Powder, Pearl Powder, Propylene Carbonate, Disodium EDTA,
Amethyst Powder, Tourmaline, Triethoxycaprylylsilane, Sodium Hyaluronate, Platinum Powder, Astaxanthin

DESCRIPTION

Directions: After applying B.B Boomer, apply an appropriate amount evenly over the face. Highlight T-zone and underneath eye area to accentuate facial contour.
Caution: For external use only. Do not swallow. Keep out of reach of children. Avoid contact with eyes